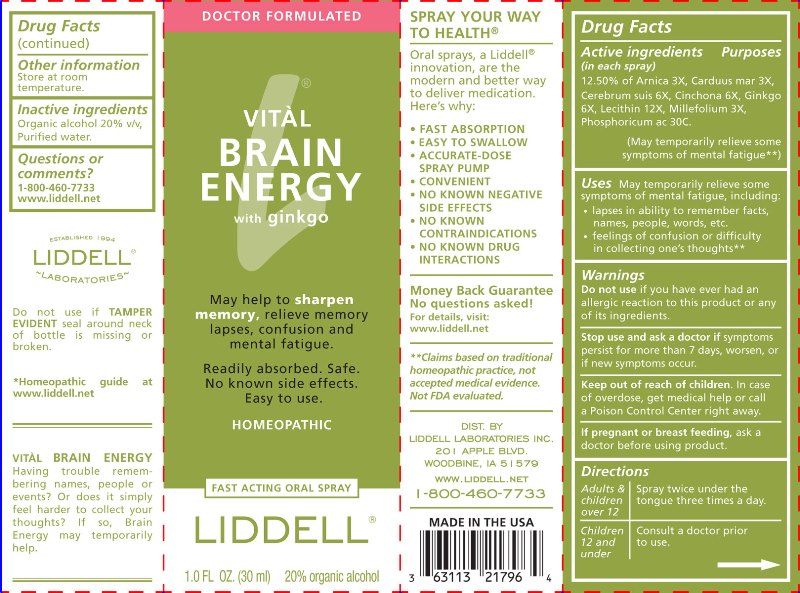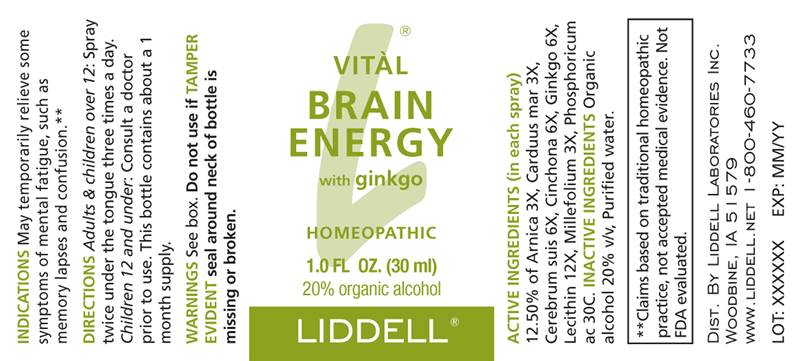 DRUG LABEL: Vital Brain Energy
NDC: 50845-0231 | Form: SPRAY
Manufacturer: Liddell Laboratories, Inc.
Category: homeopathic | Type: HUMAN OTC DRUG LABEL
Date: 20241104

ACTIVE INGREDIENTS: ARNICA MONTANA WHOLE 3 [hp_X]/1 mL; MILK THISTLE 3 [hp_X]/1 mL; SUS SCROFA CEREBRUM 6 [hp_X]/1 mL; CINCHONA OFFICINALIS BARK 6 [hp_X]/1 mL; GINKGO 6 [hp_X]/1 mL; LECITHIN, SOYBEAN 12 [hp_X]/1 mL; ACHILLEA MILLEFOLIUM WHOLE 3 [hp_X]/1 mL; PHOSPHORIC ACID 30 [hp_C]/1 mL
INACTIVE INGREDIENTS: WATER; ALCOHOL

DRUG FACTS:

ACTIVE INGREDIENTS:

(in each spray) 12.50% of Arnica Montana 3X, Carduus Marianus 3X, Cerebrum Suis 6X, Cinchona Officinalis 6X, Ginkgo Biloba 6X, Lecithin 12X, Millefolium 3X, Phosphoricum Acidum 30C.

PURPOSE:

May temporarily relieve some symptoms of mental fatigue, such as memory lapses and confusion.**

**Claims based on traditional homeopathic practice, not accepted medical evidence. Not FDA evaluated.

WARNINGS:

Do not use if you have ever had an allergic reaction to this product or any of its ingredients.

Stop use and ask a doctor if symptoms persist, worsen or if new symptoms occur.

Keep out of reach of children. In case of overdose, get medical help or call a Poison Control Center right away.

If pregnant or breast feeding, ask a doctor before use.

Do not use if TAMPER EVIDENT seal around neck of bottle is missing or broken.

Keep out of reach of children. In case of overdose, get medical help or call a Poison Control Center right away.

DIRECTIONS:

Adults and children over 12: Spray twice under the tongue three times a day.

Children 12 and under: Consult a doctor prior to use.

USES:

May temporarily relieve some symptoms of mental fatigue, including:

- lapses in ability to remember facts, names, people, words, etc.
- feelings of confusion or difficulty in collecting one's thoughts**

**Claims based on traditional homeopathic practice, not accepted medical evidence. Not FDA evaluated.

INACTIVE INGREDIENTS:

Organic alcohol 20% v/v, Purified water.

QUESTIONS:

DIST. BY
LIDDELL LABORATORIES INC.
201 APPLE BLVD.
WOODBINE, IA 51579
WWW.LIDDELL.NET
1-800-460-7733

PACKAGE LABEL DISPLAY:

DOCTOR FORMULATED

VITAL BRAIN ENERGY

with ginkgo

May help to sharpen memory,

relieve memory lapses,

confusion and mental fatigue.

Readily absorbed. Safe.

No known side effects. Easy to use.

HOMEOPATHIC

FAST ACTING ORAL SPRAY

LIDDELL

1.0 FL OZ. (30 ml)